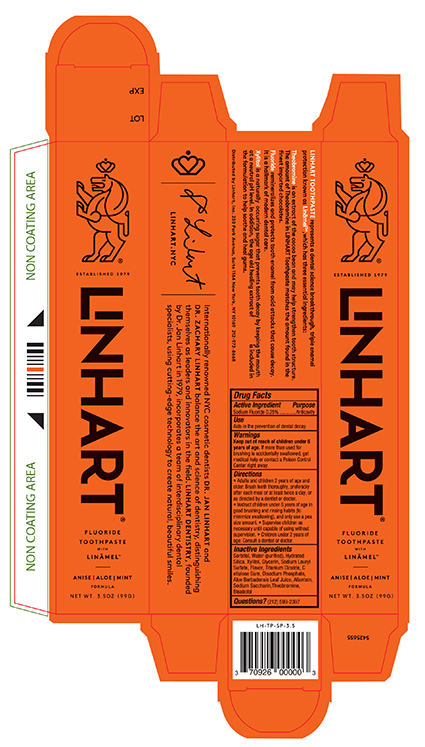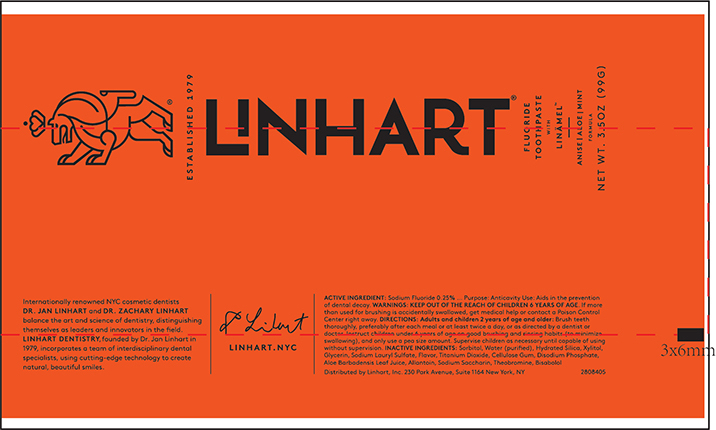 DRUG LABEL: Linhart
NDC: 70926-100 | Form: PASTE, DENTIFRICE
Manufacturer: Linhart Inc
Category: otc | Type: HUMAN OTC DRUG LABEL
Date: 20210322

ACTIVE INGREDIENTS: SODIUM FLUORIDE 2.5 mg/1 g
INACTIVE INGREDIENTS: SORBITOL; WATER; HYDRATED SILICA; XYLITOL; GLYCERIN; SILICON DIOXIDE; SODIUM LAURYL SULFATE; TITANIUM DIOXIDE; CARBOXYMETHYLCELLULOSE; SODIUM PHOSPHATE DIBASIC DIHYDRATE; ALOE VERA LEAF; ALLANTOIN; SACCHARIN SODIUM; .ALPHA.-BISABOLOL, (+/-)-; THEOBROMINE

Active ingredient

Sodium Fluoride 0.25%

Purpose

Anticavity

Uses

Aids in the prevention of tooth decay

Warnings

If more than used for brushing is accidentally swallowed, get medical help or contact a Poison control center right away.

Directions

- Adults and Children 2 years of age and older: Brush teeth thoroughly, preferably after each meal or at least twice a day, or as directed by a dentist or doctor.
- Instruct children 6 years of age in good brushing and rinsing habits (to minimize swallowing), and and only use a pea size amount.
- Supervise children as necessary until capable of using without supervision.
- Chlidren under 2 years of age: Consult a dentist or doctor.

Inactive ingredients

Sorbitol, Water (purified), Hydrated Silica, Xylitol, Glycerin, Sodium Lauryl Sulfate, Flavor, Titanium Dioxide, Cellulose gum, Disodium Phosphate, Aloe Barbadenias Leaf Juice, Allantoin, Sodium Saccharin, Theobromine, Bisabolol

Principal Primary Panel - Carton 3.5oz

LINHART with Linamel

Fluoride Toothpaste

NET WT 3.5oz(99g)

Principal Primary Panel - Tube 3.5oz

LINHART with Linamel

Fluoride Toothpaste

NET WT 3.5oz (99g)